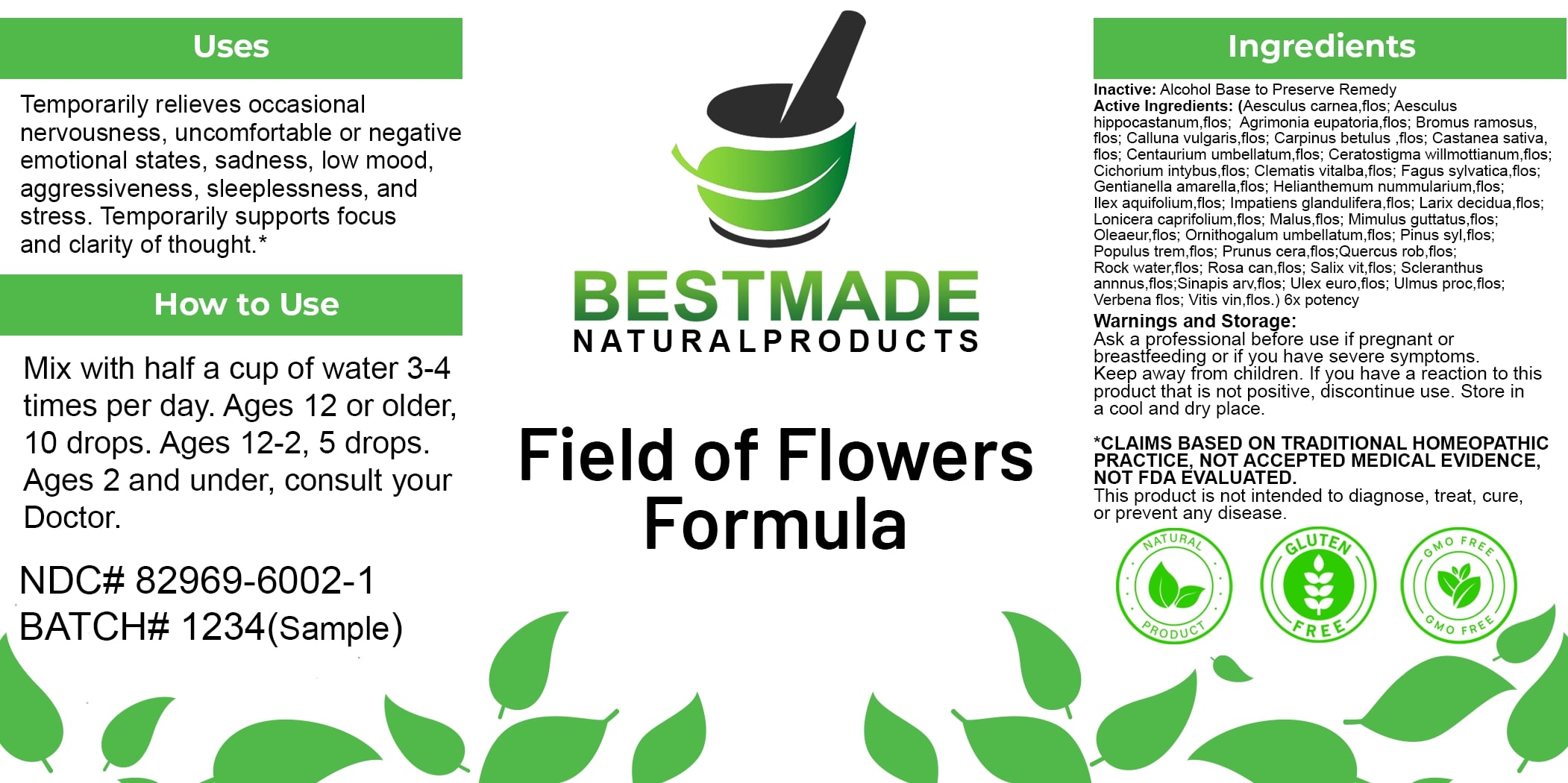 DRUG LABEL: Bestmade Natural Products Field of Flowers Formula
NDC: 82969-6002 | Form: LIQUID
Manufacturer: Bestmade Natural Products
Category: homeopathic | Type: HUMAN OTC DRUG LABEL
Date: 20250307

ACTIVE INGREDIENTS: POPULUS TREMULA FLOWERING TOP 6 [hp_X]/6 [hp_X]; SCLERANTHUS ANNUUS FLOWERING TOP 6 [hp_X]/6 [hp_X]; CICHORIUM INTYBUS FLOWER 6 [hp_X]/6 [hp_X]; CALLUNA VULGARIS FLOWERING TOP 6 [hp_X]/6 [hp_X]; CENTAURIUM ERYTHRAEA FLOWER 6 [hp_X]/6 [hp_X]; SALIX ALBA FLOWERING TOP 6 [hp_X]/6 [hp_X]; GENTIANELLA AMARELLA FLOWER 6 [hp_X]/6 [hp_X]; CERATOSTIGMA WILLMOTTIANUM FLOWER 6 [hp_X]/6 [hp_X]; HELIANTHEMUM NUMMULARIUM FLOWER 6 [hp_X]/6 [hp_X]; BROMUS RAMOSUS FLOWER 6 [hp_X]/6 [hp_X]; LONICERA CAPRIFOLIUM FLOWERING TOP 6 [hp_X]/6 [hp_X]; OLEA EUROPAEA FLOWER 6 [hp_X]/6 [hp_X]; CLEMATIS VITALBA FLOWER 6 [hp_X]/6 [hp_X]; ILEX AQUIFOLIUM FLOWERING TOP 6 [hp_X]/6 [hp_X]; MIMULUS GUTTATUS FLOWERING TOP 6 [hp_X]/6 [hp_X]; ROSA CANINA FLOWER 6 [hp_X]/6 [hp_X]; ULMUS PROCERA FLOWERING TWIG 6 [hp_X]/6 [hp_X]; FAGUS SYLVATICA FLOWERING TOP 6 [hp_X]/6 [hp_X]; ULEX EUROPAEUS FLOWER 6 [hp_X]/6 [hp_X]; LARIX DECIDUA FLOWERING TOP 6 [hp_X]/6 [hp_X]; MALUS DOMESTICA FLOWER 6 [hp_X]/6 [hp_X]; PINUS SYLVESTRIS FLOWERING TOP 6 [hp_X]/6 [hp_X]; QUERCUS ROBUR FLOWER 6 [hp_X]/6 [hp_X]; AQUA 6 [hp_X]/6 [hp_X]; PRUNUS CERASIFERA FLOWER 6 [hp_X]/6 [hp_X]; IMPATIENS GLANDULIFERA FLOWER 6 [hp_X]/6 [hp_X]; AGRIMONIA EUPATORIA FLOWER 6 [hp_X]/6 [hp_X]; ORNITHOGALUM UMBELLATUM FLOWERING TOP 6 [hp_X]/6 [hp_X]; AESCULUS HIPPOCASTANUM FLOWER 6 [hp_X]/6 [hp_X]; CARPINUS BETULUS FLOWERING TOP 6 [hp_X]/6 [hp_X]; VERBENA OFFICINALIS FLOWERING TOP 6 [hp_X]/6 [hp_X]; VITIS VINIFERA FLOWERING TOP 6 [hp_X]/6 [hp_X]; AESCULUS CARNEA FLOWER 6 [hp_X]/6 [hp_X]; CASTANEA SATIVA FLOWER 6 [hp_X]/6 [hp_X]; SINAPIS ARVENSIS FLOWERING/FRUITING TOP 6 [hp_X]/6 [hp_X]
INACTIVE INGREDIENTS: ALCOHOL 6 [hp_X]/6 [hp_X]

Field of flowers formula

DOSAGE AND ADMINISTRATION

How to Use

Take with water 3-4 times a day. Ages 12 or older, 5 Pellets, Ages 12-2, 3 Pellets, Ages below 2, consult your Doctor.

Uses

Temporarily relieves occasional nervousness, uncomfortable or negative emotional states, sadness, low mood, aggressiveness, sleeplessness, and stress. Temporarily supports focus and clarity of thought.*

*CLAIMS BASED ON TRADITIONAL HOMEOPATHIC PRACTICE, NOT ACCEPTED MEDICAL EVIDENCE. NOT FDA EVALUATED.

This product is not intended to diagnose, treat, cure, or prevent any disease.

Uses

Temporarily relieves occasional nervousness, uncomfortable or negative emotional states, sadness, low mood, aggressiveness, sleeplessness, and stress. Temporarily supports focus and clarity of thought.*

*CLAIMS BASED ON TRADITIONAL HOMEOPATHIC PRACTICE, NOT ACCEPTED MEDICAL EVIDENCE. NOT FDA EVALUATED.

This product is not intended to diagnose, treat, cure, or prevent any disease.

ACTIVE INGREDIENT

Active Ingredients: (Aesculus carnea, flos; Aesculus hippocastanum, flos; Agrimonia eupatoria, flos; Bromus ramosus, flos; Calluna vulgaris, flos; Carpinus betulus, flos; Castanea sativa, flos; Centaurium umbellatum, flos; Ceratostigma willmottianum, flos; Cichorium intybus, flos; Clematis vitalba, flos; Fagus sylvatica, flos; Gentianella amarella, flos; Helianthemum nummularium, flos; Ilex aquifolium, flos; Impatiens glandulifera, flos; Larix decidua, flos; Lonicera caprifolium, flos; Malus, flos; Mimulus guttatus, flos; Oleaeur, flos; Ornithogalum umbellatum, flos; Pinus syl, flos; Populus trem, flos; Prunus cera, flos; Quercus rob, flos; Rock water, flos; Rosa can, flos; Salix vit, flos; Scleranthus annnus, flos; Sinapis arv, flos; Ulex euro, flos; Ulmus proc, flos; Verbena flos; Vitis vin, flos.) 6x potency

INACTIVE INGREDIENT

Ingredients

Inactive: Alcohol Base to Preserve Remedy

KEEP OUT OF REACH OF CHILDREN

Warnings and Storage:

Ask a professional before use if pregnant or breastfeeding or if you have severe symptoms. Keep away from children. If you have a reaction to this product that is not positive, discontinue use. Store in a cool and dry place.

Warnings and Storage:

Ask a professional before use if pregnant or breastfeeding or if you have severe symptoms. Keep away from children. If you have a reaction to this product that is not positive, discontinue use. Store in a cool and dry place.

*CLAIMS BASED ON TRADITIONAL HOMEOPATHIC PRACTICE, NOT ACCEPTED MEDICAL EVIDENCE. NOT FDA EVALUATED.

This product is not intended to diagnose, treat, cure, or prevent any disease.

Entire package label